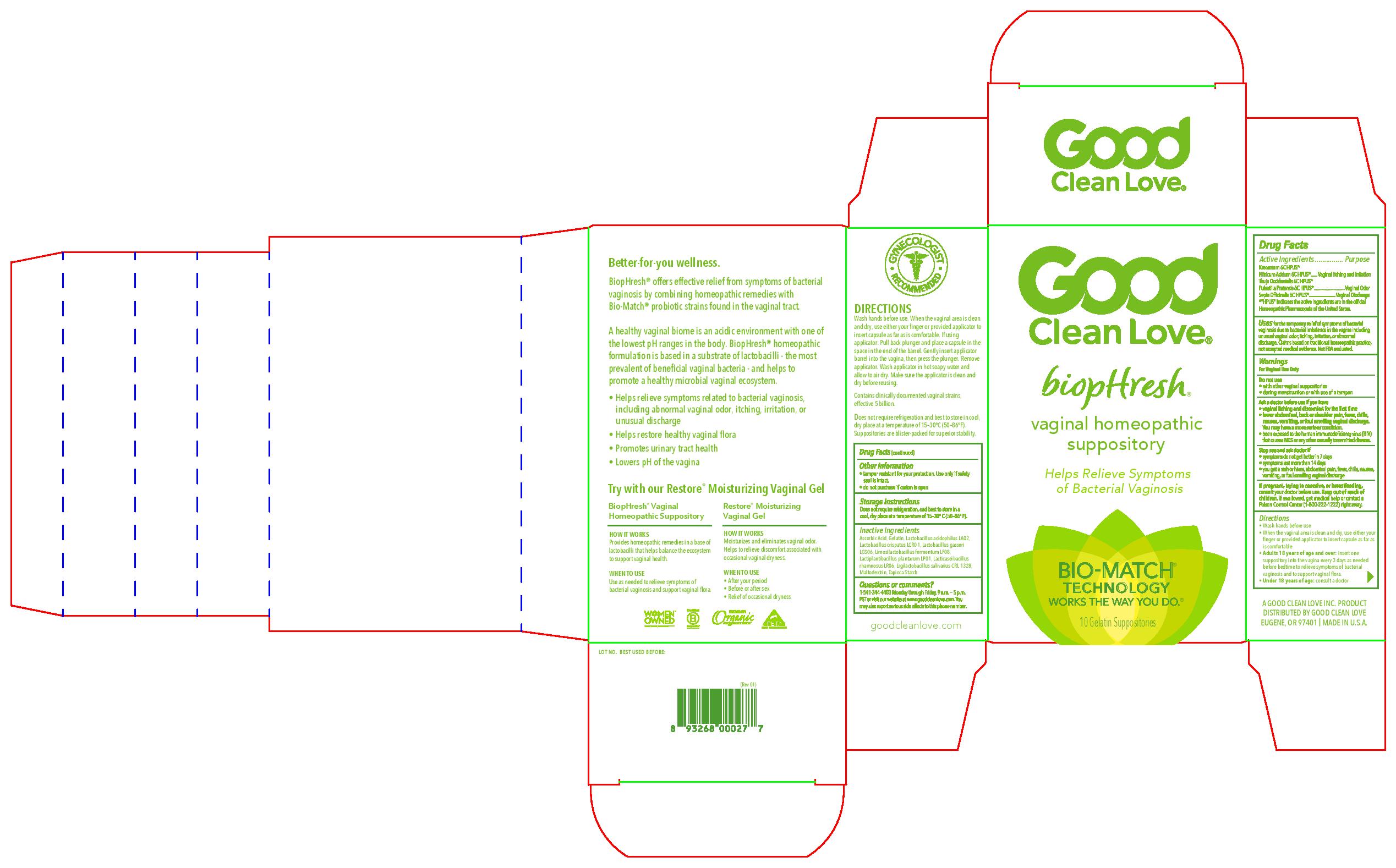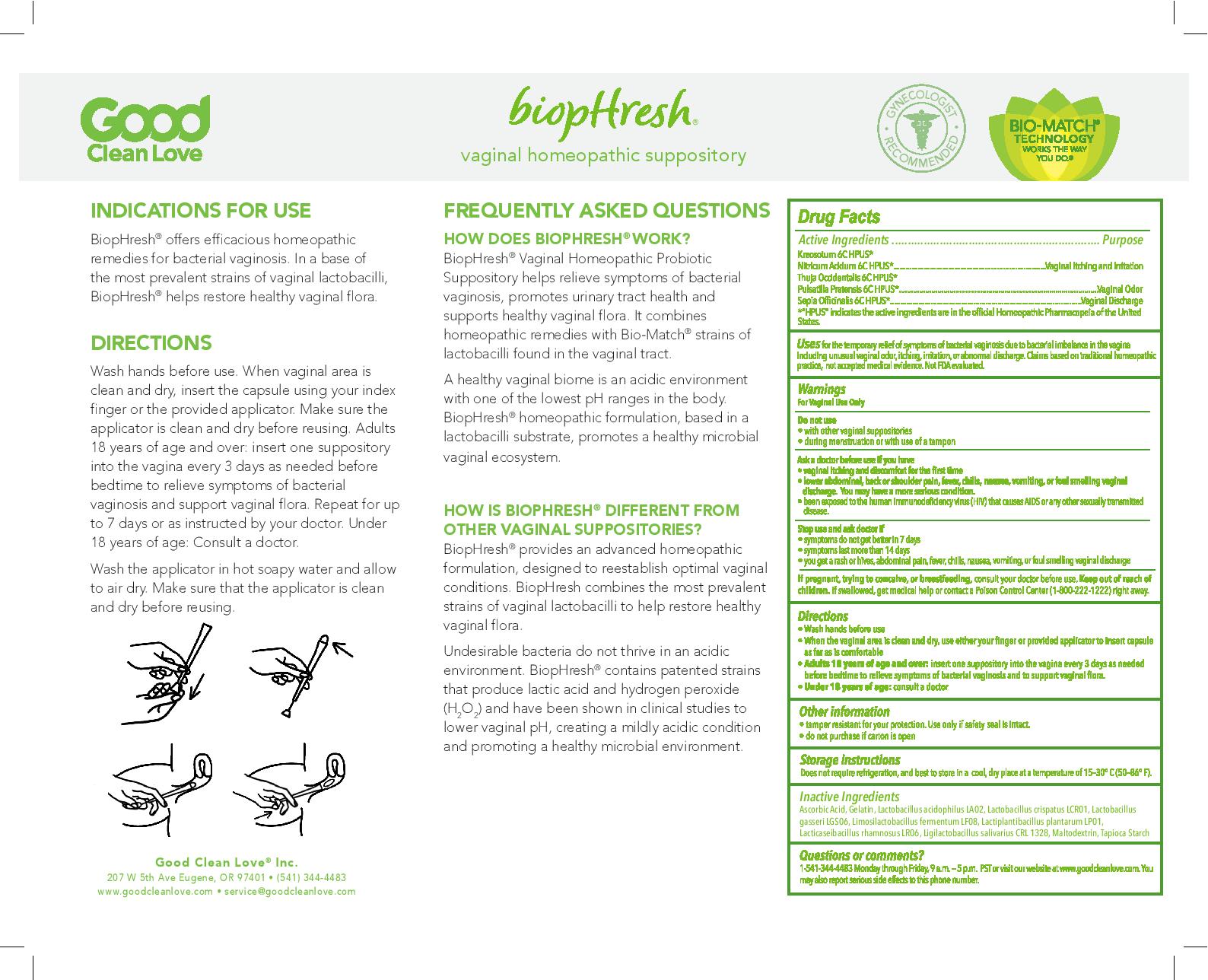 DRUG LABEL: BiopHresh
NDC: 73716-001 | Form: SUPPOSITORY
Manufacturer: Good Clean Love, Inc.
Category: homeopathic | Type: HUMAN OTC DRUG LABEL
Date: 20250707

ACTIVE INGREDIENTS: THUJA OCCIDENTALIS LEAFY TWIG 6 [hp_C]/1 g; PULSATILLA VULGARIS 6 [hp_C]/1 g; SEPIA OFFICINALIS WHOLE 6 [hp_C]/1 g; WOOD CREOSOTE 6 [hp_C]/1 g; NITRIC ACID 6 [hp_C]/1 g
INACTIVE INGREDIENTS: STARCH, TAPIOCA; LACTOBACILLUS PLANTARUM; LACTOBACILLUS RHAMNOSUS; MALTODEXTRIN; LACTOBACILLUS GASSERI; LACTOBACILLUS REUTERI; LACTOBACILLUS SALIVARIUS; ASCORBIC ACID; GELATIN; LACTOBACILLUS ACIDOPHILUS; LACTOBACILLUS CRISPATUS

BiopHresh

ACTIVE INGREDIENT

Kreosotum 6C HPUS*

Nitricum Acidum 6C HPUS*

Thuja Occidentalis 6C HPUS*

Pulsatilla Pratensis 6C HPUS*

Sepia Officinalis 6C HPUS*

*"HPUS" indicates the active ingredients are in the official Homeopathic Pharmacopeia of the United States.

PURPOSE

Kreosotum 6C HPUS*

Nitricum Acidum 6C HPUS*................Vaginal Itching and Irritation

Thuja Occidentalis 6C HPUS*

Pulsatilla Pratensis 6C HPUS*................Vaginal Odor

Sepia Officinalis 6C HPUS*................Vaginal Discharge

*"HPUS" indicates the active ingredients are in the official Homeopathic Pharmacopeia of the United States.

INDICATIONS AND USAGE

Usesfor the temporary relief of symptoms of bacterial vaginosis due to bacterial imbalance in the vagina including unusual vaginal odor, itching, irritaiton, or abnormal discharge. Claims based on traditional homeopathic practice, not accepted medical evidence. Not FDA evaluated.

WARNINGS

For Vaginal Use Only

Do not use

- with other vaginal suppositories
- during menstruation or with use of a tampon

Ask a doctor before use if you have

- vaginal itching and discomfort for the first time
- lower abdominal, back or shoulder pain, fever, chills, nausea, vomiting, or foul smelling vaginal discharge. You may have a more serious condition.
- been exposed to the human immunodeficiency virus (HIV) that causes AIDS or any other sexually transmitted disease.

Stop use and ask doctor if

- symptoms do not get better in 7 days
- symptoms last more than 14 days
- you ge a rash or hives, abdominal pain, fever, chills, nausea, vomiting, or foul smelling vaginal discharge

PREGNANCY OR BREAST FEEDING

If pregnant, trying to conceive, or breastfeedingconsult your doctor before use.

Keep out of reach of children.If swallowed, get medical help or contact a Poison Control Center (1-800-222-1222) right away.

Directions

- Wash hands before use
- When the vaginal area is clean and dry, use either your finger or providede applicator to insert capsule as far as is comfortable
- Adults 18 years of age and over:insert one suppository into the vagina every 3 days as needed before bedtime to relieve symptoms of bacterial vaginosis and to support vaginal flora.
- Under 18 years of age:consult a doctor

Other information

- tamper resistant for your protection. Use only if safety seal is intact.
- do not purchase if carton is open

Storage instructions

Does not require refrigeration, and best to store in a cool, dry place at a temperature of 15-30 C (50-86 F).

Inactive ingredients

Ascorbic Acid, Gelatin, Lactobacillus acidophilus LA02, Lactobacillus crispatus LCR01, Lactobacillus gasseri LGS06, Limosilactobacillus fermentum LF08, Lactiplantibacillus plantarum LP01, Lacticaseibacillus rhamnosus LR06, Ligilactobacillus salivarius CRL1328, Maltodextrin, Tapioca starch

Questions or comments?

1-541-344-4483 Monday through Friday, 9 a.m. - 5 p.m. PST or visit our website at www.goodcleanlove.com. You may also report serious side effects to this phone number.

PACKAGE LABEL

Good Clean Love

biopHresh

vaginal homeopathic suppositor

Helps Relieve Symptoms of Bacterial Vaginosis

BIO-MATCH TECHNOLOGY

WORKS THE WAY YOU DO.

10 Gelatin Suppositories